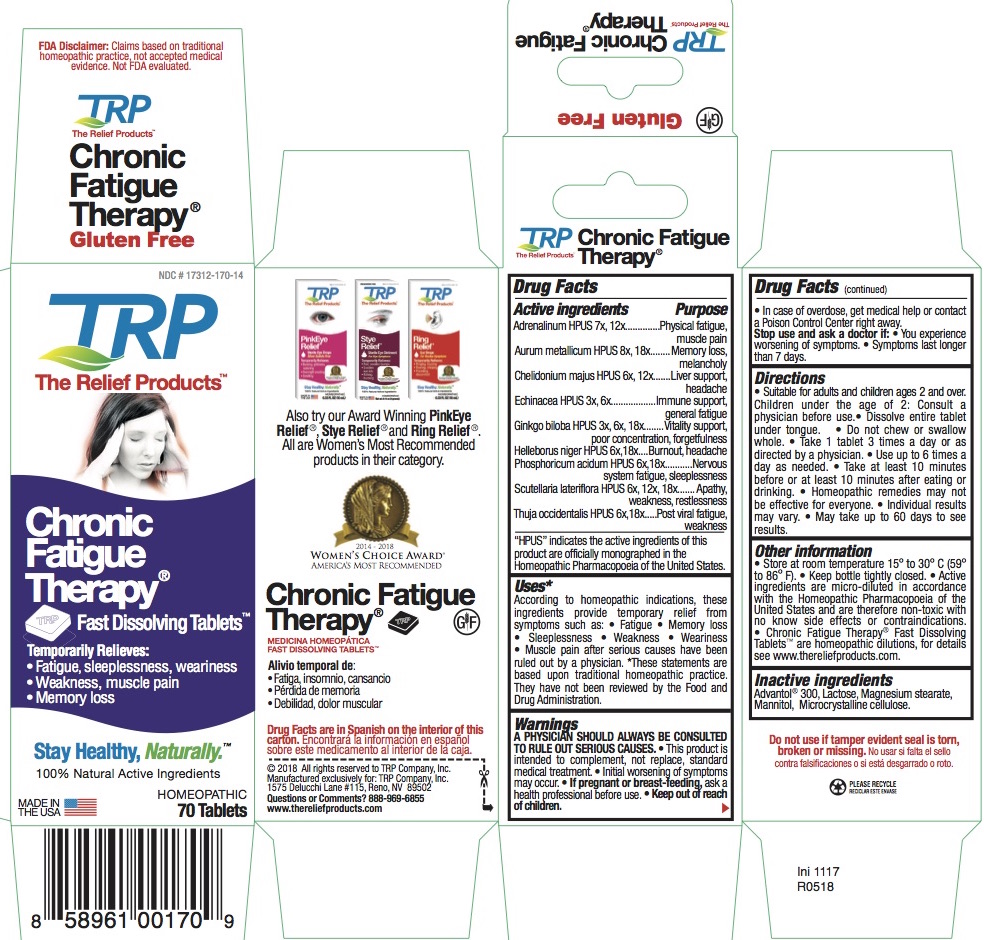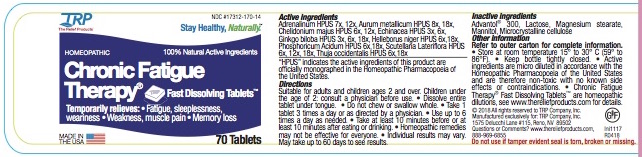 DRUG LABEL: Chronic Fatigue Therapy
NDC: 17312-170 | Form: TABLET, ORALLY DISINTEGRATING
Manufacturer: TRP Company
Category: homeopathic | Type: HUMAN OTC DRUG LABEL
Date: 20251215

ACTIVE INGREDIENTS: SCUTELLARIA LATERIFLORA 6 [hp_X]/1 1; THUJA OCCIDENTALIS LEAFY TWIG 6 [hp_X]/1 1; GINKGO 3 [hp_X]/1 1; CHELIDONIUM MAJUS 6 [hp_X]/1 1; EPINEPHRINE 7 [hp_X]/1 1; PHOSPHORIC ACID 6 [hp_X]/1 1; ECHINACEA, UNSPECIFIED 3 [hp_X]/1 1; GOLD 8 [hp_X]/1 1; HELLEBORUS NIGER ROOT 6 [hp_X]/1 1
INACTIVE INGREDIENTS: MANNITOL; SORBITOL; CROSPOVIDONE; CELLULOSE, MICROCRYSTALLINE; COPOVIDONE; SILICON DIOXIDE; LACTOSE; MAGNESIUM STEARATE

Chronic Fatigue Therapy Fast Dissolving Tablets

ACTIVE INGREDIENT

Adrenalinum HPUS 7x, 12x

Aurum metallicum HPUS 8x, 18x
Chelidonium majus HPUS 6x, 12x
Echinacea HPUS 3x, 6x
Ginkgo biloba HPUS 3x, 6x, 18x
Helleborus niger HPUS 6x,18x
Phosphoricum acidum HPUS 6x,18x
Scutellaria lateriflora HPUS 6x, 12x, 18x
Thuja occidentalis HPUS 6x,18x

HPUS indicates the active ingredients are in the Homeopathic Pharmacopoeia of the United States.

PURPOSE

Adrenalinum HPUS..................Physical fatigue, muscle pain

Aurum metallicum HPUS .........Memory loss, melancholy
Chelidonium majus HPUS........Liver support, headache
Echinacea HPUS......................Immune support, general fatigue
Ginkgo biloba HPUS.................Vitality support, poor concentration, forgetfulness
Helleborus niger HPUS.............Burnout, headache
Phosphoricum acidum HPUS....Nervous system fatigue, sleeplessness
Scutellaria lateriflora HPUS...... Apathy, weakness, restlessness
Thuja occidentalis HPUS...........Post viral fatigue, weakness

Uses

According to homeopathic indications, these ingredients provide temporary relief from symptoms such as: • Fatigue • Memory loss • Sleeplessness • Weakness • Weariness • Muscle pain after serious causes have been ruled out by a physician.

*These statements are based upon traditional homeopathic practice. They have not been reviewed by the Food and Drug Administration.

Warnings

A PHYSICIAN SHOULD ALWAYS BE CONSULTED TO RULE OUT SERIOUS CAUSES.

• This product is intended to complement, not replace, standard medical treatment.

• Initial worsening of symptoms may occur .

Stop use

Stop use and ask a doctor if:

• You experience worsening of symptoms.

• Symptoms last longer than 7 days.

PREGNANCY OR BREAST FEEDING

If pregnant or breast-feeding, ask a health professional before use.

Keep out of reach of children

• In case of overdose, get medical help or contact a Poison Control Center right away.

Directions

- Suitable for adults and children ages 2 and over. Children under the age of 2: Consult a physician before use.
- Dissolve entire tablet under tongue.
- Do not chew or swallow whole. • Take 1 tablet 3 times a day or as directed by a physician.
- Use up to 6 times a day as needed.
- Take at least 10 minutes before or at least 10 minutes after eating or drinking.
- Homeopathic remedies may not be effective for everyone. •
- Individual results may vary.
- May take up to 60 days to see results.

Other information

- Store at room temperature 15o to 30o C (59o to 86o F).
- Keep bottle tightly closed. • Active ingredients are micro-diluted in accordance with the Homeopathic Pharmacopoeia of the United States and are therefore non-toxic with no know side effects or contraindications.
- Chronic Fatigue Therapy® Fast Dissolving TabletsTM are homeopathic dilutions, for details see www.thereliefproducts.com.

Inactive Ingredients

Advantol® 300, Lactose, Magnesium Stearate, Mannitol, Microcrystalline Cellulose.

Questions or comments? www.thereliefproducts.com, 888-969-6855

PACKAGE LABEL

FDA Disclaimer: Claims based on traditional homeopathic practice, not accepted medical evidence. Not FDA evaluated.